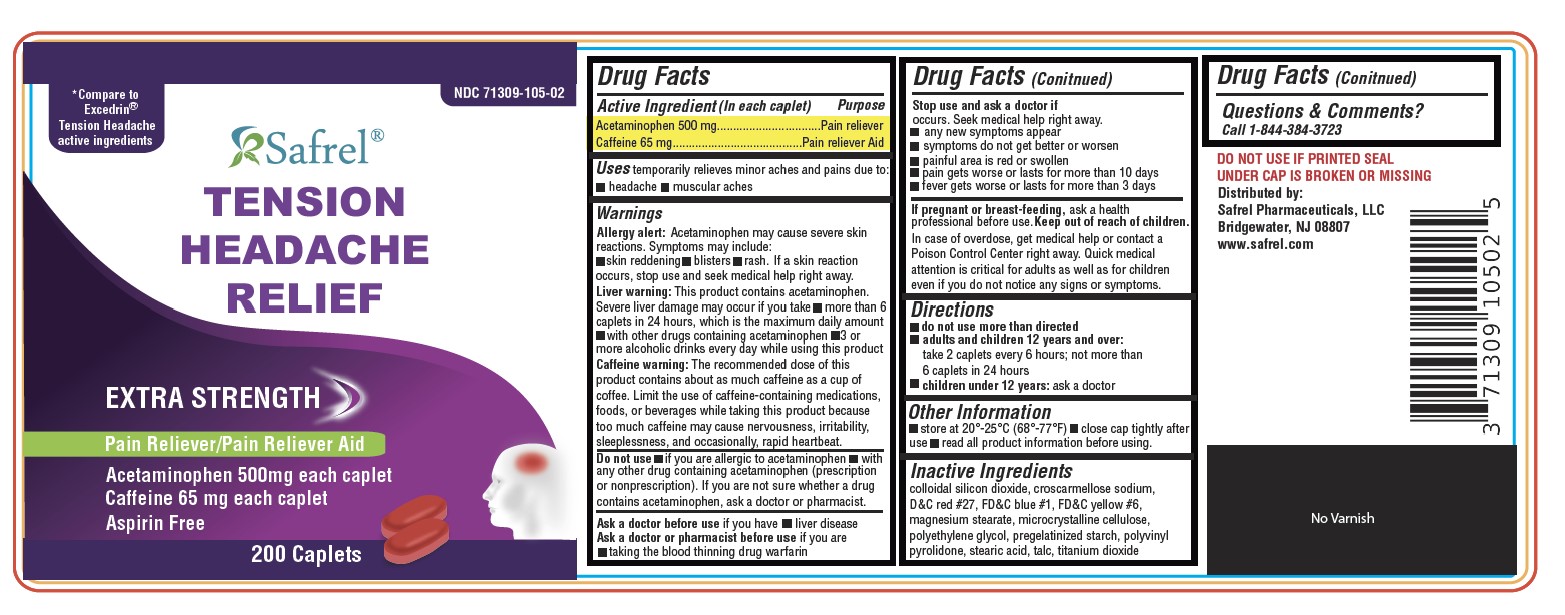 DRUG LABEL: Tension Headache Relief
NDC: 71309-105 | Form: TABLET, COATED
Manufacturer: Safrel Pharmaceuticals, LLC.
Category: otc | Type: HUMAN OTC DRUG LABEL
Date: 20210531

ACTIVE INGREDIENTS: ACETAMINOPHEN 500 mg/1 1; CAFFEINE 65 mg/1 1
INACTIVE INGREDIENTS: SILICON DIOXIDE; CROSCARMELLOSE SODIUM; D&C RED NO. 27; FD&C BLUE NO. 1; FD&C YELLOW NO. 6; MAGNESIUM STEARATE; MICROCRYSTALLINE CELLULOSE; STARCH, PREGELATINIZED CORN; STEARIC ACID; TALC; TITANIUM DIOXIDE; POLYETHYLENE GLYCOL, UNSPECIFIED; POVIDONE

Tension Headache Relief

Drug Facts

Tension Headache Relief

Purpose

Pain reliever, Pain reliever aid

Active Ingredients (in each caplet)

Acetaminophen 500mg

Caffeine 65mg

Uses

Temporarily relief minor aches and pains due to:

- Headache
- Muscular aches

Warnings

Liver warning: This product contains acetaminophen. severe liver damage may occur if you take:

- more than 6 tablets in 24 hours, which is the maximum daily amount
- with other drugs containing acetaminophen
- 3 or more alcoholic drinks every day while using this product

Caffeine warning: The recommended dose of this product contains about as much caffeine as a cup of coffee. Limit the use of caffeine-containing medications, foods, or beverages while taking this product because too much caffeine may cause nervousness, irritability, sleeplessness, and occasionally rapid heartbeat.

Do not Use

- with any other drug containing acetaminophen (prescription or nonprescription). Ask a doctor or pharmacist before using with other drugs if you are not sure.

Ask a doctor before use

- if you have liver disease

Ask a doctor or pharmacist

If you are taking the blood thinning drug warfarin.

Stop use and ask a doctor if

- Any new symptoms appear
- Symptoms do not get better or worsen
- Painful area is red or swollen
- pain gets worse or lasts for more than 10 days
- fever gets worse or lasts for more than 3 days

If pregnant or breast-feeding

Ask a health professional before use.

Keep out of reach of children.

In case of overdosage, get medical help or contact a Poison Control Center (1-800-222-1222) right away. Quick medical attention is critical for adults as well as for children even if you do not notice any signs or symptoms.

Directions

- Do not exceed recommended dosage.
- Adults and children 12 years and over: Take 2 tablets every 6 hours; do not take more than 6 tablets in 24 hours
- Children under 12 years: Ask a doctor

Other Information

- Store at controlled room temperature 20°-25°C (68°-77°F)
- TAMPER EVIDENT: DO NOT USE IF IMPRINTED SAFETY SEAL UNDER CAP

Inactive Ingredients

- Colloidal silicon doixide
- Croscarmellose sodium
- D&C red # 27
- FD&C blue # 1
- FD&C yellow # 6
- Magnesium stearate
- Microcrystalline cellulose
- Polyethylene glycol
- Pregelatinized starch
- Polyvinyl pyrolidone
- Stearic acid
- Talc
- Titanium dioxide

Questions or comments?

Call toll free 1-844-384-3723 Monday through Friday 9AM - 5PM EST or www.safrel.com